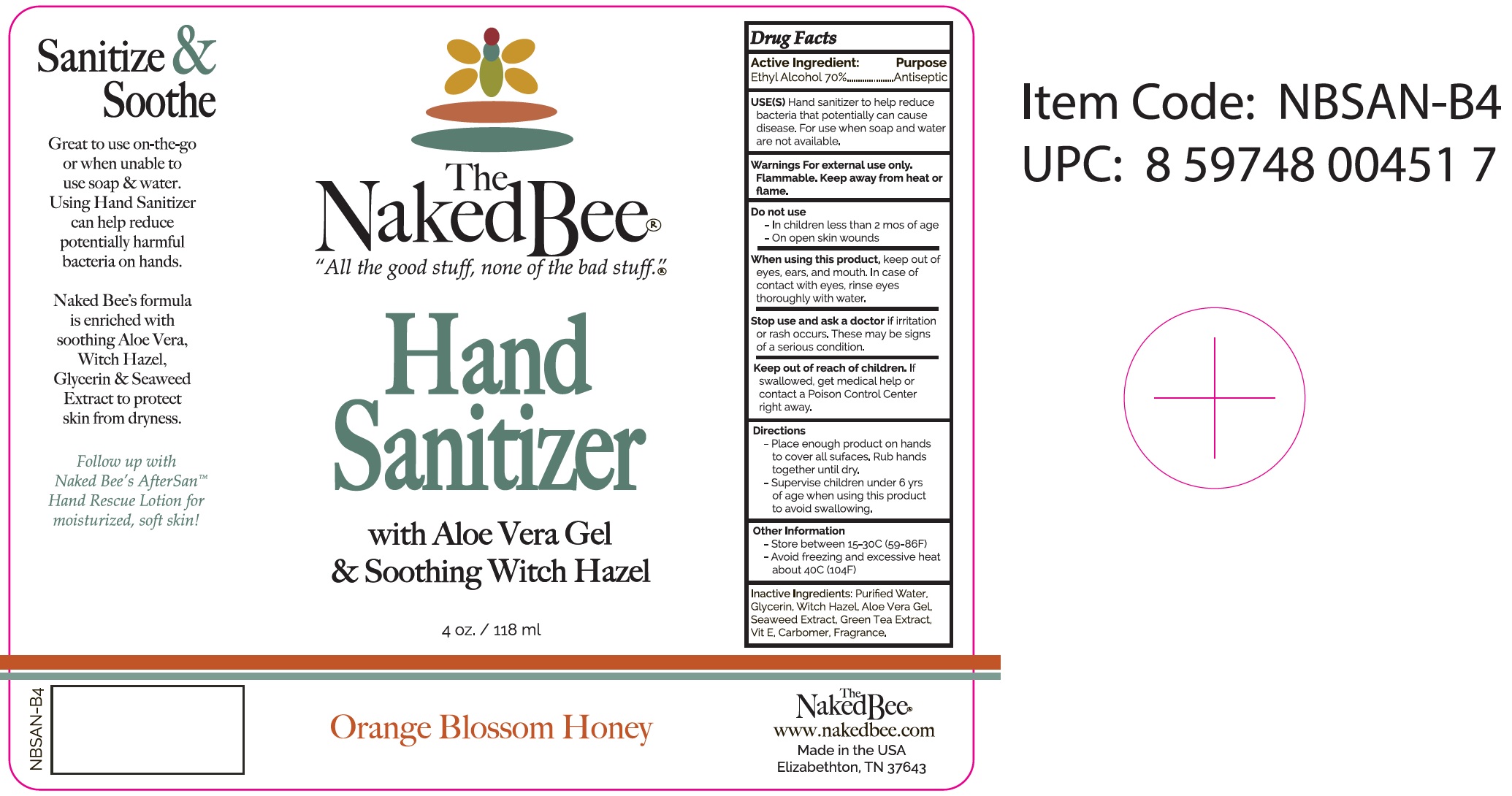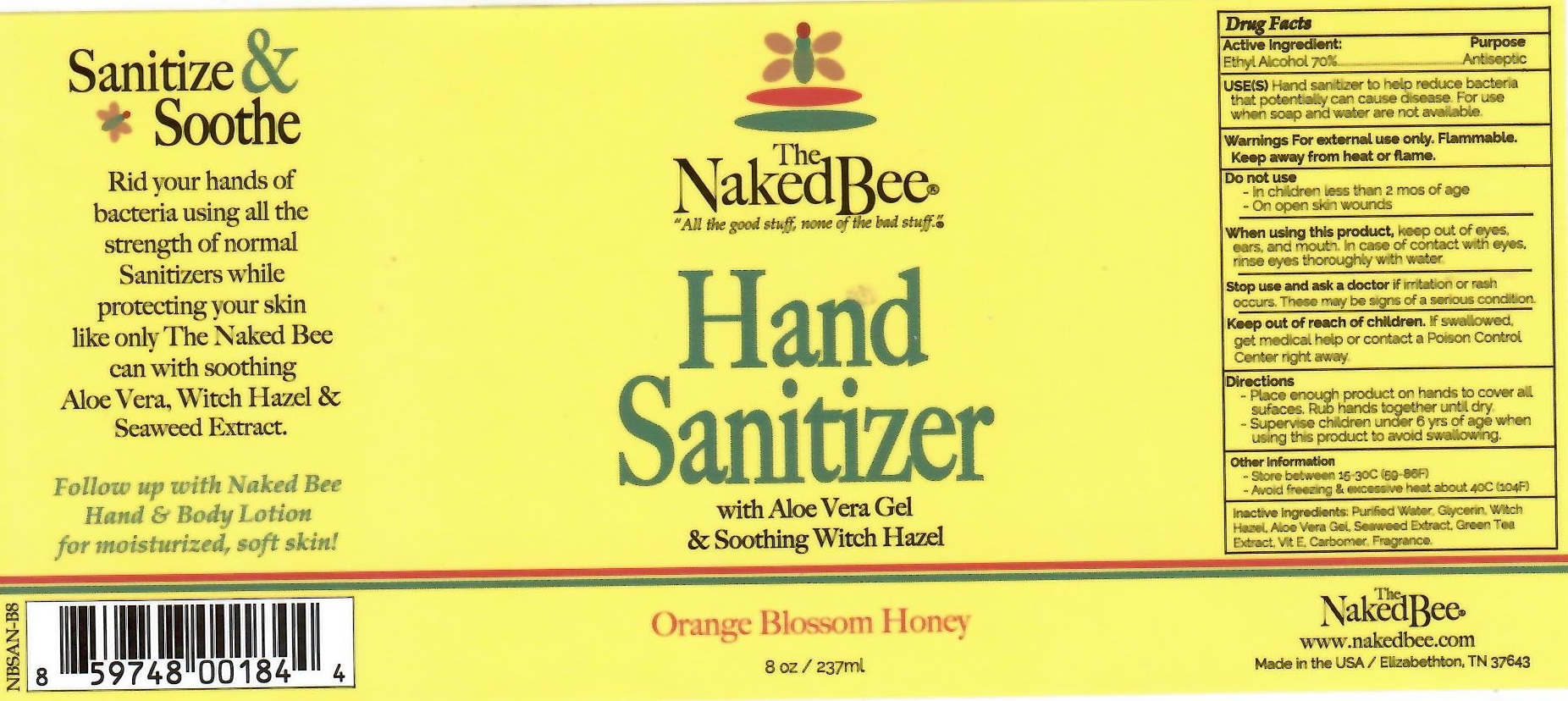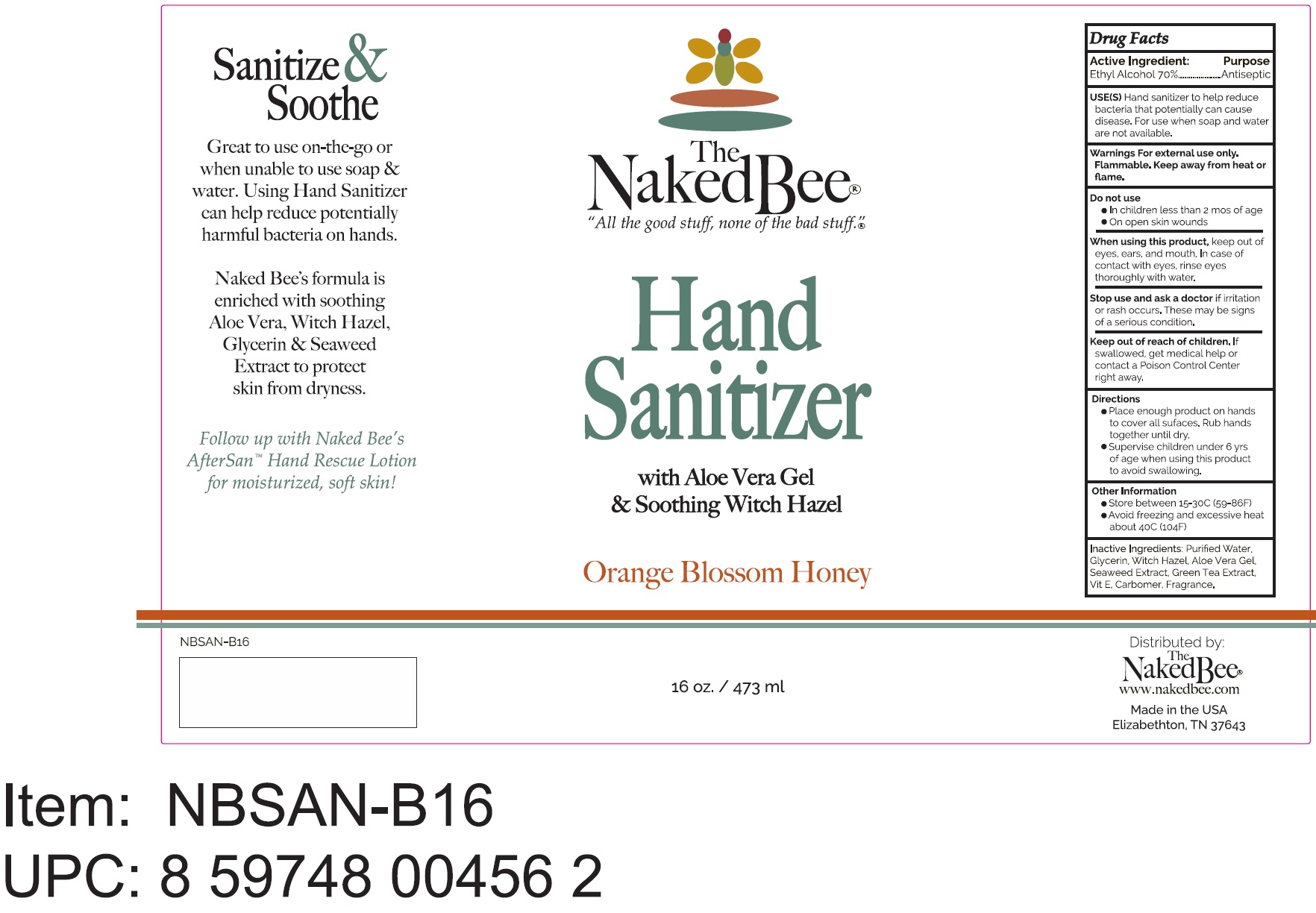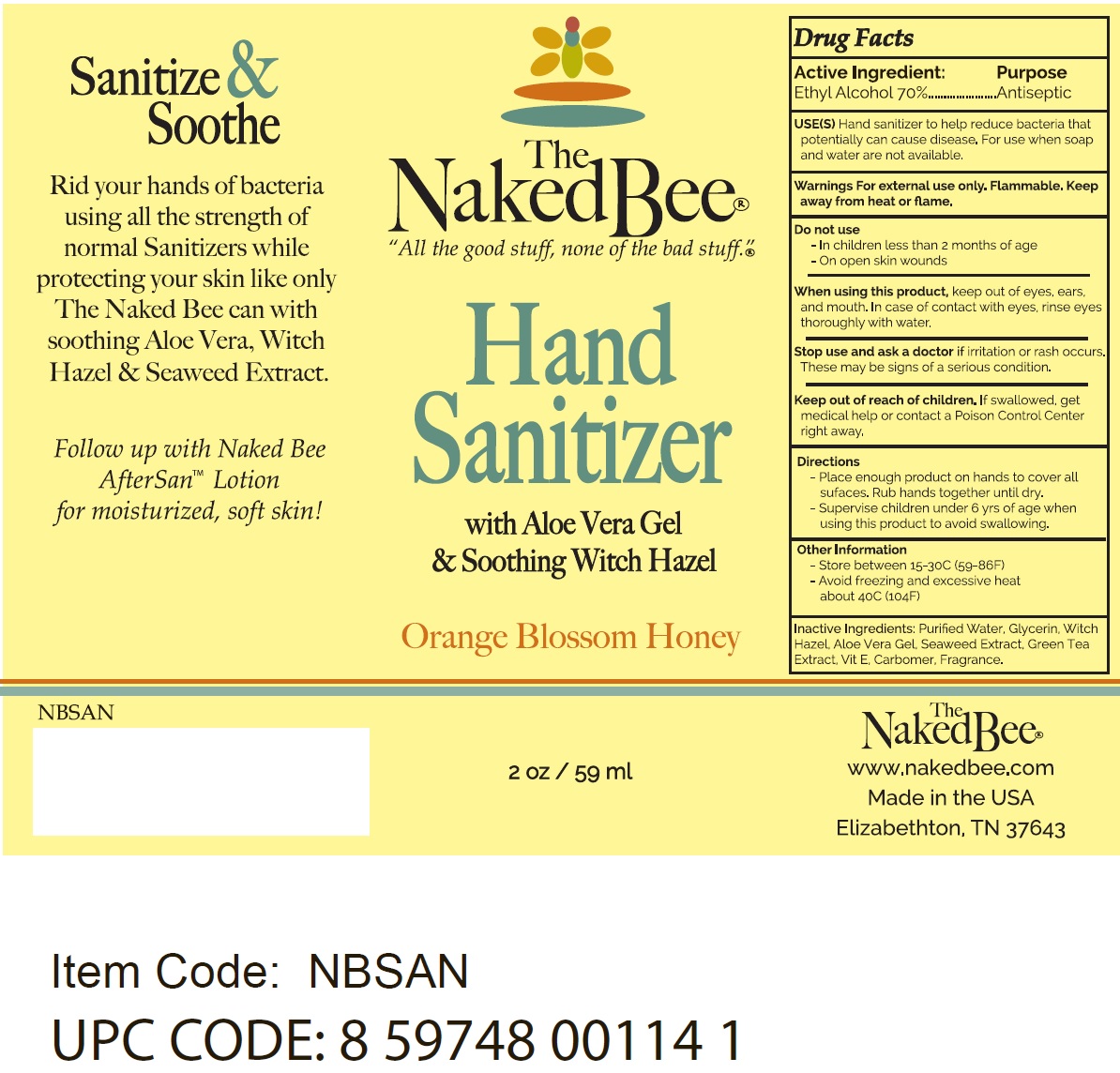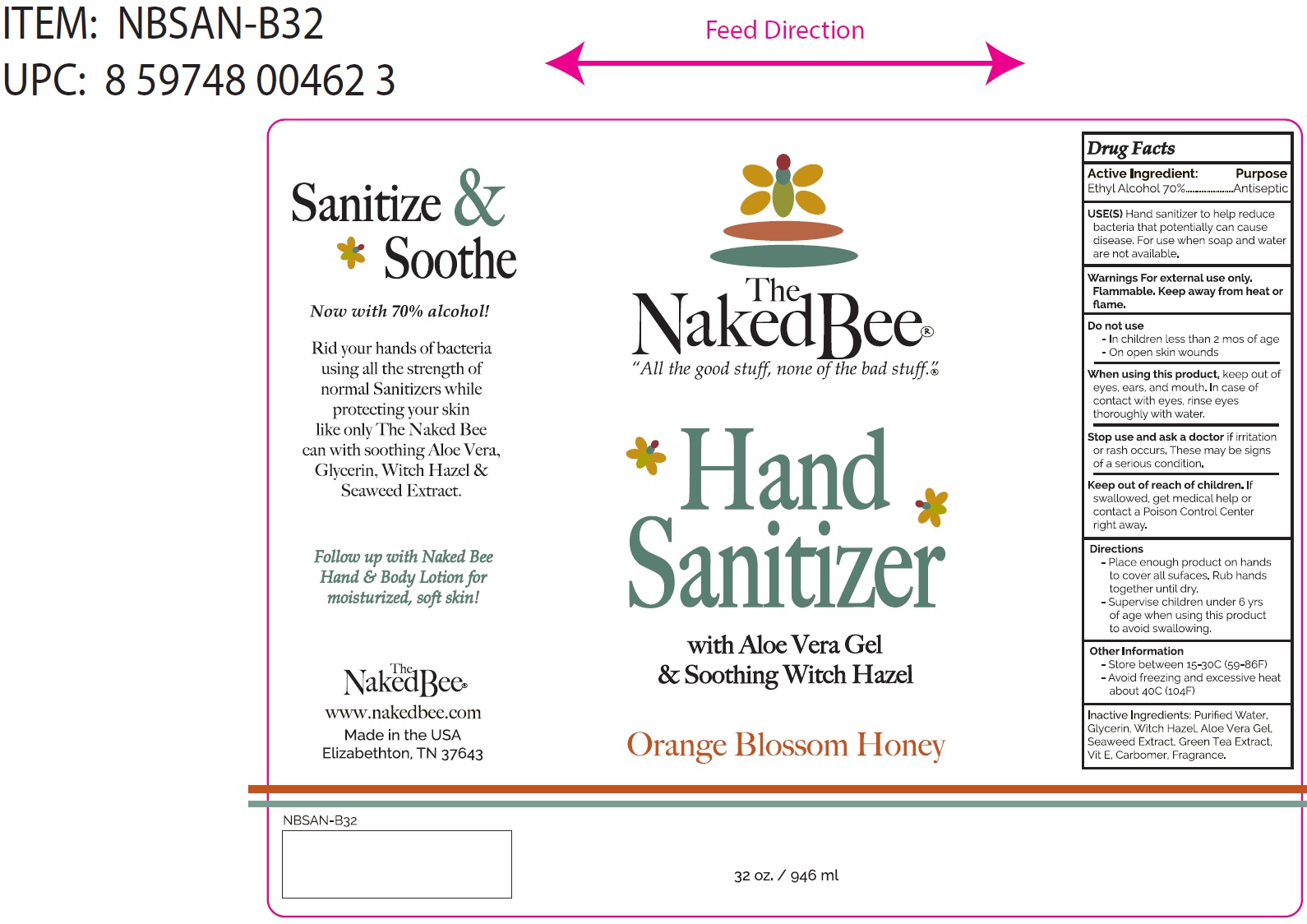 DRUG LABEL: The Naked Bee Hand Sanitizer Orange Blossom Honey
NDC: 82820-000 | Form: GEL
Manufacturer: The Naked Bee
Category: otc | Type: HUMAN OTC DRUG LABEL
Date: 20220705

ACTIVE INGREDIENTS: ALCOHOL 70 mL/100 mL
INACTIVE INGREDIENTS: WATER; GLYCERIN; WITCH HAZEL; ALOE VERA LEAF; GREEN TEA LEAF; CARBOMER HOMOPOLYMER, UNSPECIFIED TYPE

The Naked Bee Hand Sanitizer Orange Blossom Honey

Active Ingredient:

Ethyl Alcohol 70%

Purpose

Antiseptic

USE(S)

Hand sanitizer to help reduce bacteria that potentially can cause disease, For use when soap and water are not available.

Warnings

For external use only. Flammable. Keep away from heat or flame.

Do not use

- In children less than 2 months of age

- On open skin wounds

When using this product,

keep out of eyes, ears, and mouth. In case of contact with eyes. rinse eyes thoroughly with water.

Stop use and ask a doctor

if irritation or rash occurs. These may be signs of a serious condition.

Keep out of reach of children.

If swallowed, get medical help or contact a Poison Control Center right away.

Directions

- Place enough product on hands to cover all sufaces. Rub hands together until dry.

- Supervise children under 6 yrs of age when using this product to avoid swallowing.

Other Information

- Store between 15-30C (59-86)

- Avoid freezing and excessive heat about 40C (104F)

Package Labeling:

Purified Water, Glycerin, Witch Hazel, Aloe Vera Gel, Seaweed Extract, Green Tea Extract, Vit E, Carbomer, Fragrance.